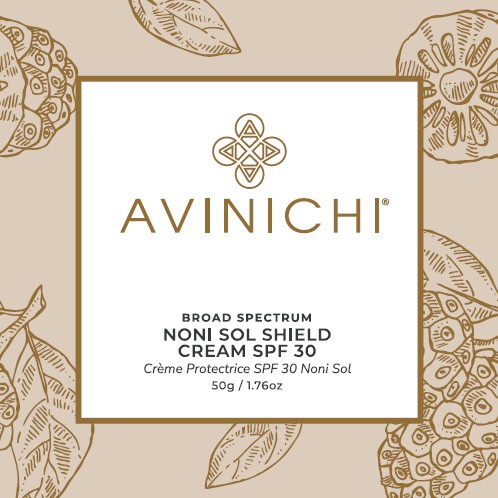 DRUG LABEL: Avinichi Noni Sol Shield Cream SPF 30
NDC: 72104-582 | Form: CREAM
Manufacturer: Innovation Brands Inc.
Category: otc | Type: HUMAN OTC DRUG LABEL
Date: 20251030

ACTIVE INGREDIENTS: OCTINOXATE 7.4 g/100 g; HOMOSALATE 6.2 g/100 g; OCTISALATE 5.0 g/100 g; OXYBENZONE 3.1 g/100 g; AVOBENZONE 1.5 g/100 g
INACTIVE INGREDIENTS: WATER; ALKYL (C12-15) BENZOATE; GLYCERIN; GLYCERYL MONOSTEARATE; STEARIC ACID; PEG-100 MONOSTEARATE; PHENOXYETHANOL; ETHYLHEXYLGLYCERIN; POLYSORBATE 60; CARBOMER INTERPOLYMER TYPE A (ALLYL SUCROSE CROSSLINKED); CARBOMER HOMOPOLYMER, UNSPECIFIED TYPE; TROLAMINE; TOCOPHEROL; VITAMIN A PALMITATE; ALOE VERA LEAF; GREEN TEA LEAF; SODIUM PYRROLIDONE CARBOXYLATE; NONI FRUIT JUICE; EDETATE DISODIUM

AVINICHI® NONI SOL SHIELD CREAM SPF 30

Active Ingredients

Octinoxate 7.40%
Homosalate 6.20%
Octisalate 5.00%
Oxybenzone 3.10%
Avobenzone 1.50%

Purpose

Sunscreen

Uses

- Helps prevent sunburn.

Warnings

For external use only. Do not use on damaged or broken skin.

Keep out of eyes. If contact occurs, rinse with water. If rash or irritation develops, discontinue use and consult your physician.

Stop using this product

and ask doctor if rash or redness develops and lasts.

Keep out of reach of children.

If accidental ingestion, call the Poison Control Center right away.

Directions

- After cleansing, apply liberally and evenly 15 minutes before sun exposure.
  Smooth over face and neck and chest daily for optimal results.
- Reapply at least every two (2) hours.
- Use water resistant sunscreen if swimming or sweating.

Sun Protection Measures. Spending time in the sun increases your risk of skin cancer and early skin aging. To decrease this risk, regularly use a sunscreen with a Broad Spectrum SPF value of 15 or higher and other sun protection measures including:

- limit time in the sun, especially from 10 a.m.-2 p.m.
- wear long-sleeved shirts, pants, hats and sunglasses.

For children under 6 months of age: Ask doctor.

Other Information

Protect the product in this container from excessive heat and direct sun. Store at room temperature.

Inactive Ingredients

Aqua, C12-15 Alkyl Benzoate, Glycerin, Glyceryl Stearate, Stearic Acid, PEG-100 Stearate, Phenoxyethanol, Ethylhexylglycerin, Polysorbate 60, Acrylates/C10-30 Alkyl Acrylate Crosspolymer, Carbomer, Triethanolamine, Fragrance, Tocopherol, Retinyl Palmitate, Aloe Barbadensis Leaf Extract, Camellia Sinensis Extract, Sodium PCA, Morinda Citrifolia (Noni) Fruit Extract, Disodium EDTA.

Package/Label Principal Display Panel – Carton Label

AVINICHI®

BROAD SPECTRUM
NONI SOL SHIELD
CREAM SPF 30
Crème Protectrice SPF 30 Noni Sol
50g ǀ 1.76oz

WWW.AVINICHI.COM
20255 Corisco St.
Chatsworth, CA 91311